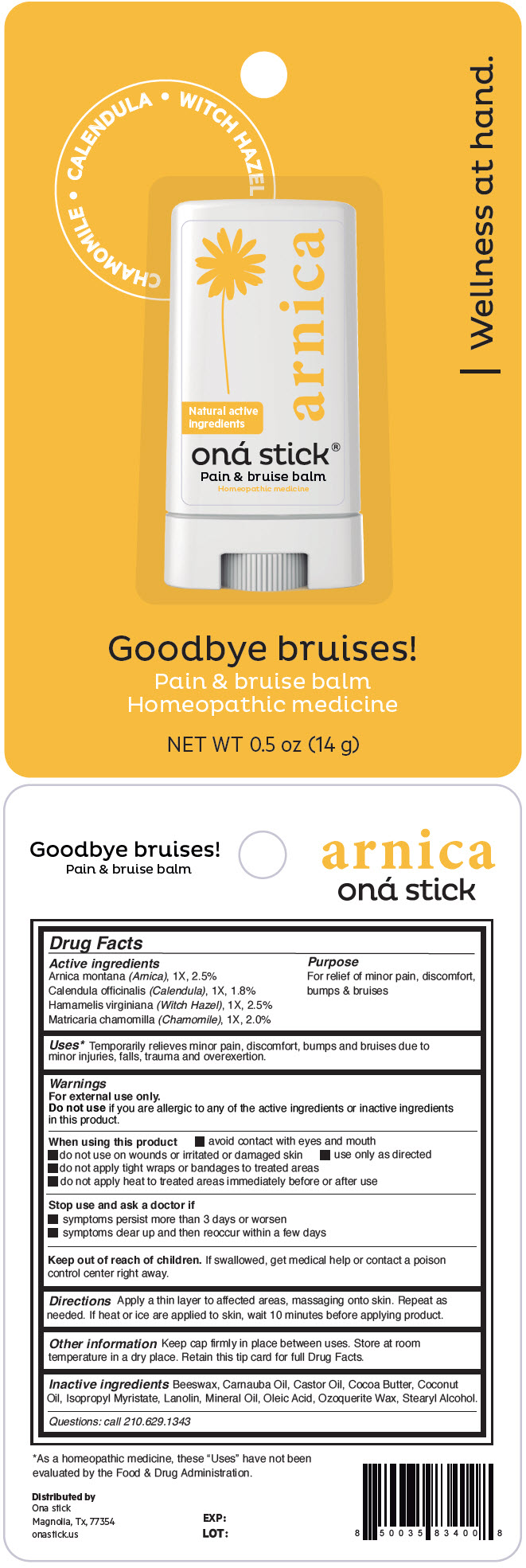 DRUG LABEL: ARNICA
NDC: 82610-003 | Form: STICK
Manufacturer: ONA STICK USA LLC
Category: homeopathic | Type: HUMAN OTC DRUG LABEL
Date: 20220317

ACTIVE INGREDIENTS: ARNICA MONTANA FLOWER 1 [hp_X]/14 g; CALENDULA OFFICINALIS FLOWER 1 [hp_X]/14 g; HAMAMELIS VIRGINIANA LEAF 1 [hp_X]/14 g; CHAMOMILE 1 [hp_X]/14 g
INACTIVE INGREDIENTS: YELLOW WAX; CARNAUBA WAX; CASTOR OIL; Cocoa Butter; Coconut Oil; Isopropyl Myristate; Lanolin; Mineral Oil; Oleic Acid; CERESIN; Stearyl Alcohol

ARNICA

Drug Facts

ACTIVE INGREDIENT

Active ingredients | Purpose
Arnica montana (Arnica), 1X, 2.5% Calendula officinalis (Calendula), 1X, 1.8% Hamamelis virginiana (Witch Hazel), 1X, 2.5% Matricaria chamomilla (Chamomile), 1X, 2.0% | For relief of minor pain, discomfort, bumps & bruises

Uses [As a homeopathic medicine, these "Uses" have not been evaluated by the Food & Drug Administration.]

Temporarily relieves minor pain, discomfort, bumps and bruises due to minor injuries, falls, trauma and overexertion.

Warnings

For external use only.

Do not use if you are allergic to any of the active ingredients or inactive ingredients in this product.

When using this product

- avoid contact with eyes and mouth
- do not use on wounds or irritated or damaged skin
- use only as directed
- do not apply tight wraps or bandages to treated areas
- do not apply heat to treated areas immediately before or after use

Stop use and ask a doctor if

- symptoms persist more than 3 days or worsen
- symptoms clear up and then reoccur within a few days

Keep out of reach of children. If swallowed, get medical help or contact a poison control center right away.

Directions

Apply a thin layer to affected areas, massaging onto skin. Repeat as needed. If heat or ice are applied to skin, wait 10 minutes before applying product.

Other information

Keep cap firmly in place between uses. Store at room temperature in a dry place. Retain this tip card for full Drug Facts.

Inactive ingredients

Beeswax, Carnauba Oil, Castor Oil, Cocoa Butter, Coconut Oil, Isopropyl Myristate, Lanolin, Mineral Oil, Oleic Acid, Ozoquerite Wax, Stearyl Alcohol.

Questions

call 210.629.1343

Distributed by
Ona stick
Magnolia, Tx, 77354

PRINCIPAL DISPLAY PANEL - 14 g Tube Blister Pack

CHAMOMILE • CALENDULA • WITCH HAZEL

Natural active
ingredients

arnica

oná stick®
Pain & bruise balm
Homeopathic medicine

| Wellness at hand.

Goodbye bruises!

Pain & bruise balm
Homeopathic medicine

NET WT 0.5 oz (14 g)